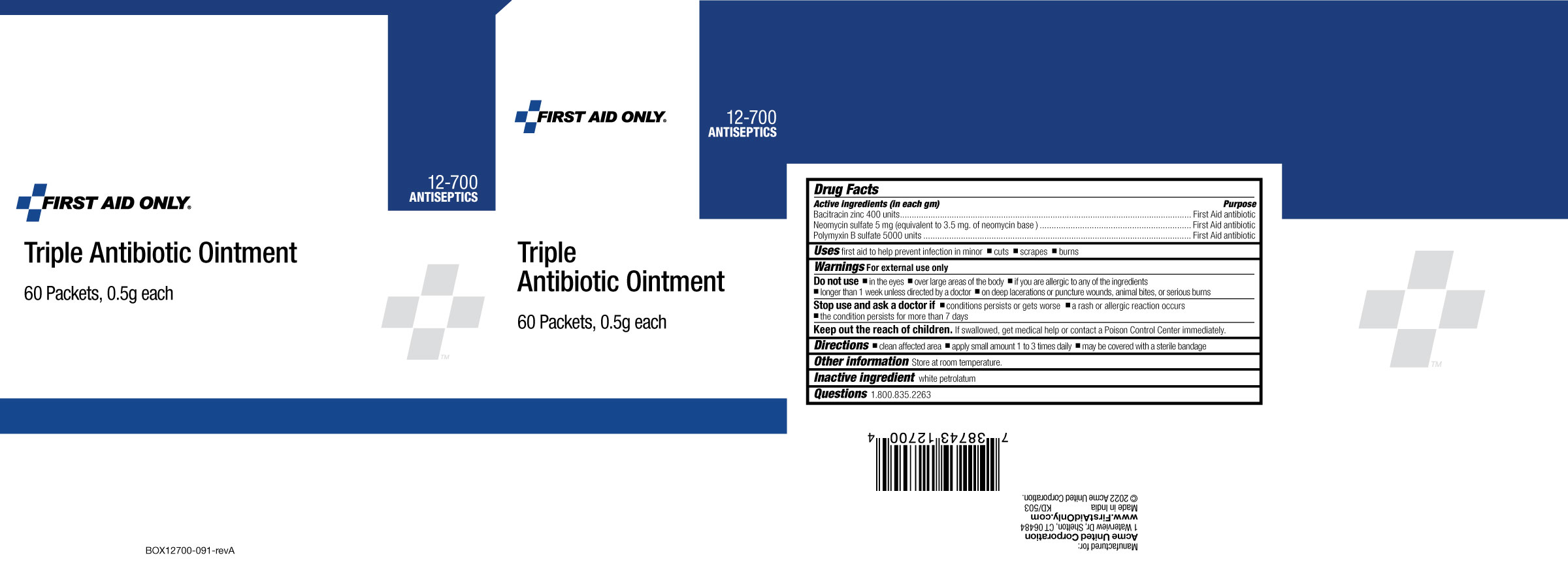 DRUG LABEL: First Aid Only Triple Antibiotic
NDC: 0924-5618 | Form: OINTMENT
Manufacturer: Acme United Corporation
Category: otc | Type: HUMAN OTC DRUG LABEL
Date: 20241119

ACTIVE INGREDIENTS: BACITRACIN ZINC 400 U/1 g; NEOMYCIN SULFATE 5 mg/1 g; POLYMYXIN B SULFATE 5000 U/1 g
INACTIVE INGREDIENTS: WHITE PETROLATUM

First Aid Only Triple Antibiotic Ointment

Active Ingredients (in each gram)

Bacitracin zinc 400 units

Neomycin sulfate 5 mg (equivalent to 3.5 mg of neomycin base)

Polymyxin B sulfate 5000 units

Purpose

First Aid Antibiotic

Uses

first aid to help prevent infection in minor •cuts, •scrapes •burns

Warnings

For external use only

Do not use

- In the eyes
- over large areas of the body
- If you are allergic to any of the ingredients
- longer than 1 week unless directed by a doctor
- on deep lacerations or puncture wounds, animal bites, or serious burns

Stop use and ask a doctor if

- condition persists or gets worse
- a rash or allergic reaction occurs
- the condition persists for more than 7 days

Keep out of reach of children.

If swallowed, get medical help or contact a Poison Control Center immediately.

Directions

- clean the affected area
- apply small amount 1 to 3 times daily
- may be covered with a sterile bandage

Other Information

Store at room temperature

Inactive Ingredient

white petrolatum

Questions

1.800.835.2263

Box Label